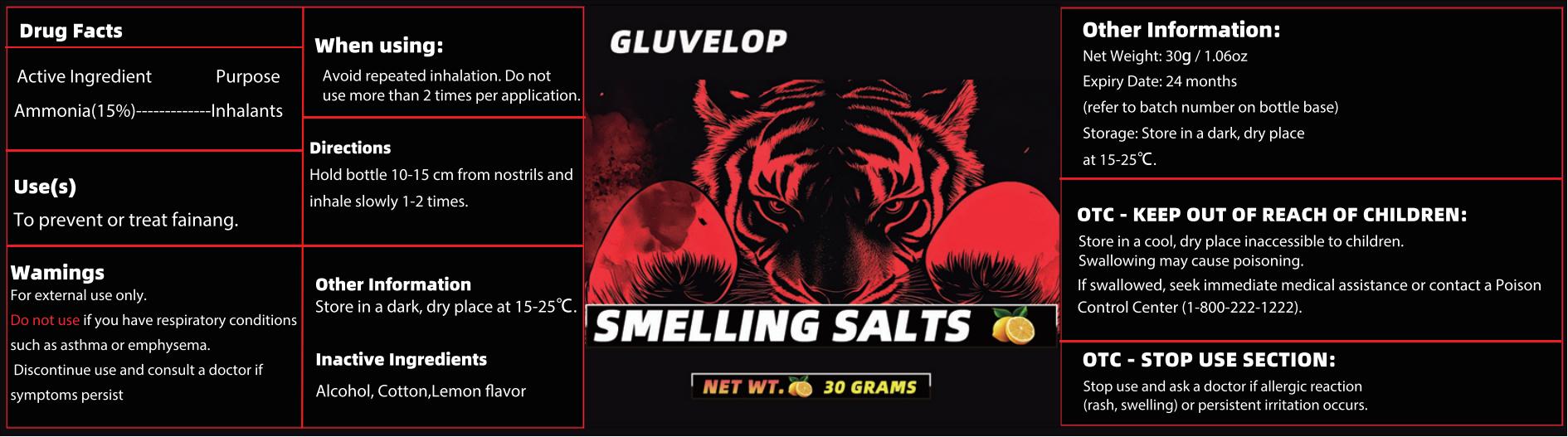 DRUG LABEL: Gluvelop SMELLING SALTS
NDC: 85590-002 | Form: INHALANT
Manufacturer: Shenzhen Nanjun Technology Co., Ltd
Category: otc | Type: HUMAN OTC DRUG LABEL
Date: 20250709

ACTIVE INGREDIENTS: AMMONIA 15 g/100 g
INACTIVE INGREDIENTS: LIMONENE, (+/-)-; ALCOHOL; COTTON

85590-002

Active Ingredient

Ammonia 15%

Purpose

Inhalants

Use

To prevent or treat fainang.

Warnings

For external use only.

Do not use if you have respiratory conditions such as asthma or emphysema.
Discontinue use and consult a doctor if symptoms persist

When Using

Avoid repeated inhalation. Do not use more than 2 times per application.

Stop Use

Stop use and ask a doctor if allergic reaction (rash, swelling) or persistent irritation occurs.

Ask Doctor

Do not use if you have respiratory conditions such as asthma or emphysema.
Discontinue use and consult a doctor if symptoms persist.

Keep Out Of Reach Of Children

Store in a cool, dry place inaccessible to children. Swallowing may cause poisoning.
If swallowed, seek immediate medical assistance or contact a Poison
Control Center(1-800-222-1222).

Directions

Hold bottle 10-15 cm from nostrils and inhale slowly 1-2 times.

Other information

Net Weight: 30g/1.06oz
Expiry Date: 24 months(refer to batch number on bottle base)
Storage: Store in a dark, dry place at 15-25°C.

Inactive ingredients

Alcohol, Cotton,Lemon flavor

Questions

Ifswallowed,seekimmediatemedicalassistanceorcontactaPoison
ControlCenter(1-800-222-1222)